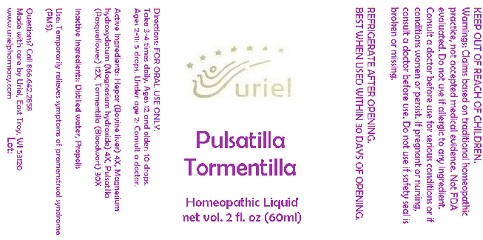 DRUG LABEL: Pulsatilla Tormentilla
NDC: 48951-8099 | Form: LIQUID
Manufacturer: Uriel Pharmacy Inc.
Category: homeopathic | Type: HUMAN OTC DRUG LABEL
Date: 20180430

ACTIVE INGREDIENTS: MAMMAL LIVER 4 [hp_X]/1 mL; MAGNESIUM HYDROXIDE 4 [hp_X]/1 mL; PULSATILLA VULGARIS 12 [hp_X]/1 mL; POTENTILLA ERECTA ROOT 30 [hp_X]/1 mL
INACTIVE INGREDIENTS: WATER; PROPOLIS WAX

Pulsatilla Tormentilla

INDICATIONS AND USAGE

Directions: FOR ORAL USE ONLY.

DOSAGE AND ADMINISTRATION

Take 3-4 times daily. Ages 12 and older: 10 drops. Ages 2-11: 5 drops. Under age 2: Consult a doctor.

ACTIVE INGREDIENT

Active Ingredients: Hepar (Bovine liver) 4X, Magnesium hydroxydatum (Magnesium hydroxide) 4X, Pulsatilla (Pasqueflower) 12X, Tormentilla (Bloodwort) 30X

Inactive Ingredients: Distilled water, Propolis

PURPOSE

Use: Temporarily relieves symptoms of premenstrual syndrome (PMS).

KEEP OUT OF REACH OF CHILDREN.

WARNINGS

Warnings: Claims based on traditional homeopathic practice, not accepted medical evidence. Not FDA evaluated. Do not use if allergic to any ingredient. Consult a doctor before use for serious conditions or if conditions worsen or persist. If pregnant or nursing, consult a doctor before use. Do not use if safety seal is broken or missing.

REFRIGERATE AFTER OPENING.
BEST WHEN USED WITHIN 30 DAYS OF OPENING.

QUESTIONS

Questions? Call 866.642.2858 Made with care by Uriel, East Troy, WI 53120 www.urielpharmacy.com